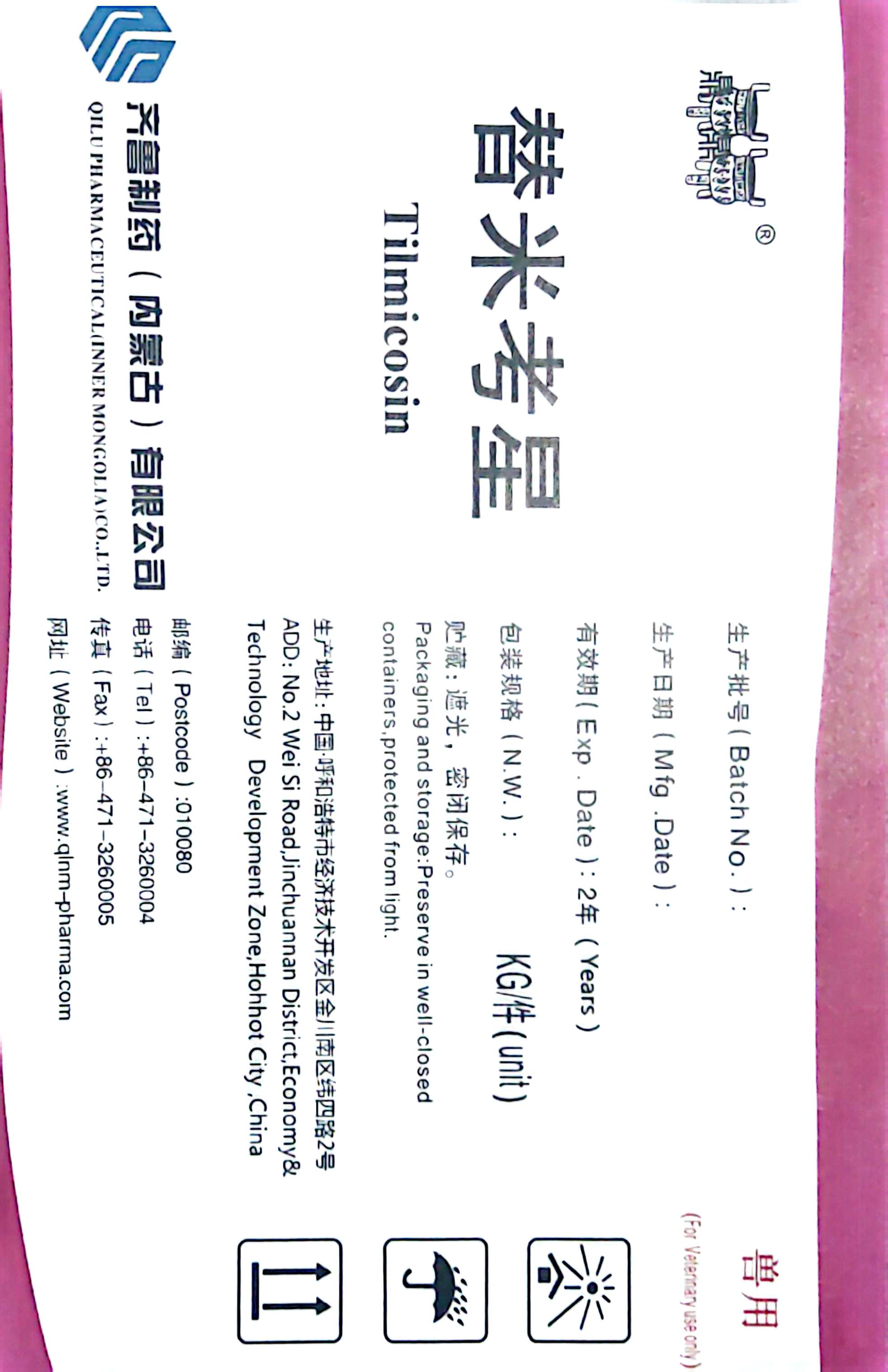 DRUG LABEL: Tilmicosin
NDC: 86098-0003 | Form: POWDER
Manufacturer: Qilu Pharmaceutical (Inner Mogolia) Co., Ltd.
Category: other | Type: BULK INGREDIENT - ANIMAL DRUG
Date: 20251121

ACTIVE INGREDIENTS: TILMICOSIN 15 kg/15 kg

Tilmicosin

PACKAGE LABEL

Tilmicosin

QILU PHARMACEUTICAL (INNER MONGOLIA) CO.,LTD.

Batch No.

Mfg,date:

Exp.date: 2 Years

N.W.: KG/unit

Packaging and storage: Preserve in well-closed containers, protected from light.

Add: No. 2 Wei Si Road, Jinchuannan District , Economy and Technology Development Zone, Hohhot City, China

Postcode: 010080

Tel:+86-471-3260004

Fax:+86-471-3260005

Website: www.qlnm-pharma.com